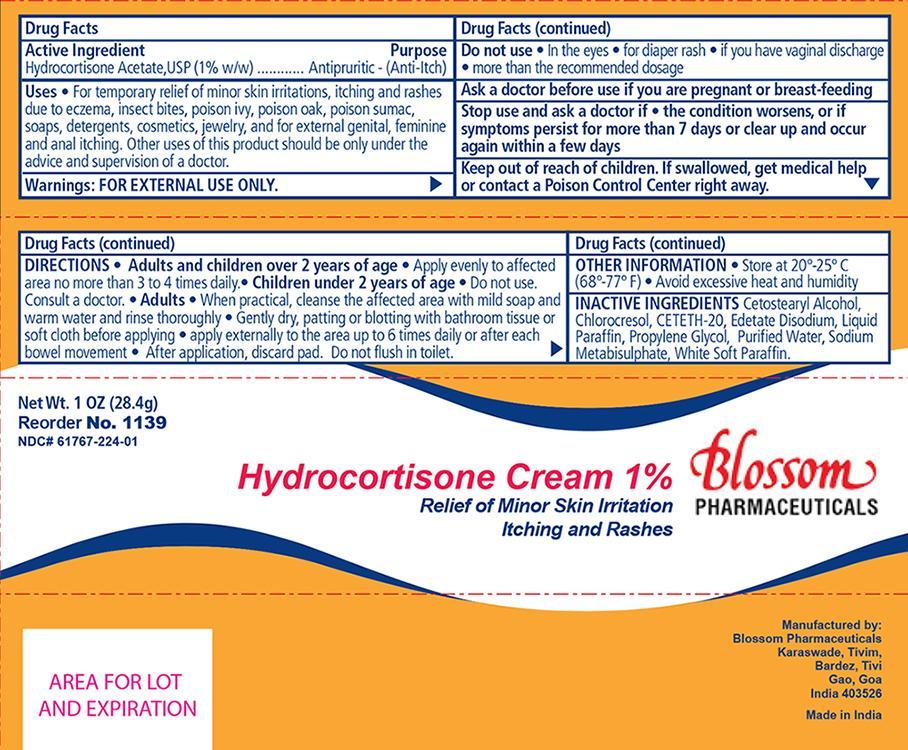 DRUG LABEL: Hydrocortisone
NDC: 61767-224 | Form: CREAM
Manufacturer: Blossom Pharmaceuticals
Category: otc | Type: HUMAN OTC DRUG LABEL
Date: 20140515

ACTIVE INGREDIENTS: HYDROCORTISONE ACETATE 1 g/100 g
INACTIVE INGREDIENTS: PROPYLENE GLYCOL; WATER; CETETH-20; CETOSTEARYL ALCOHOL; CHLOROCRESOL; EDETATE DISODIUM; MINERAL OIL; SODIUM METABISULFITE; PETROLATUM

Blossom Pharmaceuticals Hydrocortisone Cream 1%

Active Ingredient Purpose

Hydrocortisone Acetate 1% Antipruritic (anti-itch)

Warnings:

For external use only

Purpose

For temporary relief of;

- minor skin irritations

Itching and rashes due to;

- eczema
- insect bites
- poison ivy
- poison oak
- poison sumac
- soaps
- detergents
- cosmetics
- jewelry

and for external itching of;

- genital
- feminine and
- anal itching

Do not use:

- in the eyes
- longer than 1 week unless directed by a physician
- for diaper rash
- if you have vaginal discharge
- more than the recommended daily dosage unless directed by a doctor
- in the rectum bu using fingers or any other mechanical device or applicator

Stop use and ask a physician if:

- the condition persists or gets worse
- symptoms clear up and occur again within a few days
- you are pregnant or breast feeding

Keep out of reach of children

- If swallowed, get medical help or contact a Poison Control Center right away.

Dosage & Administration:

Adults and children over 2 years of age

- Apply evenly to affected area no more than 3 or 4 times daily.

Children under 2 years of age

- Do not use
- consult a physician

Adults

- When practical, cleanse the affected area with mild soap and warm water and rinse thoroughly
- Gently dry, patting and blotting with bathroom tissue or soft cloth before applying
- apply externally to the area up to 6 times daily or after each bowel movement

Other information:

- Store at 20 deg - 25 deg C (68 deg - 77 deg F)
- Avoid excessive heat and humidity

Inactive ingredients:

Cetomacrogol 1000, Cetostearyl Alcohol, Chlorocresol, Edetate Disodium, Liquid Paraffin, Propylene Glycol, Sodium Betabisulphite, White Soft Paraffin, Water (purified)

INDICATIONS AND USAGE

For temporary relief of minor skin irritations and external itching.

Principal Display Panel

Blossom Pharmaceuticals Hydrocortisone 1%

Hydrocortisone.jpg